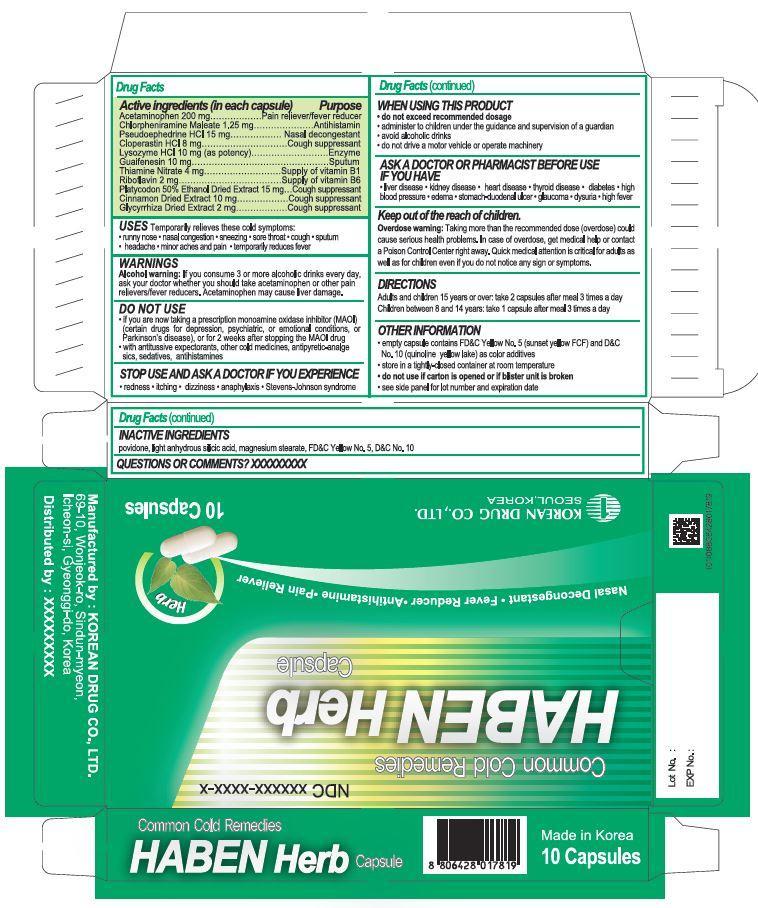 DRUG LABEL: Haben Herb
NDC: 69195-1001 | Form: CAPSULE
Manufacturer: Beverly Hills Holdings Co,. Ltd.
Category: otc | Type: HUMAN OTC DRUG LABEL
Date: 20140827

ACTIVE INGREDIENTS: CHLORPHENIRAMINE MALEATE 1.25 mg/1 1
INACTIVE INGREDIENTS: POVIDONE; MAGNESIUM STEARATE; SILICON DIOXIDE

Drug Facts

ACTIVE INGREDIENT

chlorpheniramine maleate, acetaminophen, pseudoephedrine hydrochloride, cloperastin hydrochloride, lysozyme hydrochloride, guaifenesin, thiamine nitrate, riboflavin, platycodon 50% ethanol dried extract, cinnamon dried extract, glycyrrhize dried extract

INACTIVE INGREDIENT

povidone, light anhydrous silicic acid, magnesium stearate

PURPOSE

- temporarily relieves these cold symptomes
runny nose, nasal congestion, sneezing, sore throat, cough, sputum, headache, minor aches and pain
- temporarily reduces fever

keep out of reach of the children

INDICATIONS AND USAGE

Adults and children 15 years or over: take 2 capsules after meal 3 times a day
Children between 8 and 14 years: take 1 capsule after meal 3 times a day

[DO NOT USE]
if you are hypersensitive to this drug and any component of this drug
if you have a history of asthma after taking this drug, other cold drugs or antipyreticanalgesics
in infants under 3 months of age
if you are now taking a prescription monoamine oxidase inhibitor (MAOI) (certain drugs for
depression, psychiatric, or emotional conditions, or Parkinson’s disease), or for 2 weeks after
stopping the MAOI drug
with antitussive expectorants, other cold medicines, antipyretic-analgesics, sedatives,
antihistamines(certain drugs for rhinitis, preventive drugs for travel sickness, allergies)
[ASK A DOCTOR OR PHARMACIST BEFORE USE]
in infants or children under 15 years infected with chickenpox or influenza
in infants under 2 years of age only when it is necessary. Inform to the guardian/s and
monitor closely while administering
if you are genetically prone to uticaria, contact dermatitis, bronchial asthma, allergic rhinitis,
migraine, food allergy
If you have allergic reactions (e.g., fever, rash, arthralgia, asthma, itch, etc.) to this drug and
any component of this drug
if you have liver disease, kidney disease, heart disease, thyroid disease, diabetes, high blood
pressure, edema, stomach-duodenal ulcer, glaucoma, dysuria, high fever
if you are elderly or week
if you have bleeding , ache and discomfort in stomach
If (possibly) pregnant or breast-feeding
If you are taking a prescription drug for diabetes, goat, arthritis, anticoagulants and steroids
if you have cough by smoking, asthma, chronic bronchitis, emphysema, cough accompanied
with excessive sputum, fever, rash, persistent headache and cough lasting more than 1 week,
recurrent cough or chronic cough
[STOP USE AND ASK A DOCTOR IF]
you experience any of the following symptoms:
rash, redness, itching, nausea, vomiting, loss of appetite, constipation, edema, dysuria, severe
or persistent thirst, dizziness, anxiety, shivering, insomnia
you experience any of the following severe symptoms:
anaphylaxis (e.g., immediate rash, edema, shortness of breath along with paling of face,
cold sweat, cold hands and feet)
Stevens-Johnson syndrome (mucocutaneous syndrome) or Lyell syndrome (toxic epidermal
necrosis) (e.g., rash and redness accompanied with high fever, blisters as in burn over the
body or mucous membranes of mouth or eyes) asthma
liver dysfunction (e.g., drowsiness, jaundice)
interstitial pneumonia (e.g., shortness of breath, fever accompanied with cough)
aldosteronism: long-term continuous use of preparations containing over than 1g as licorice
(daily maximum dose) may cause hypokalemia, increased blood pressure, fluid retention of
sodium, edema, weight gain, aldosteronism. Observe closely (blood potassium concentration)
and stop taking this drug and when you have above symptoms.
myopathy may rarely occur as a result of hypokalemia. Observe closely and stop taking this
drug when you appear symptoms such as weakness, limb spasms, and numbness.
[WHEN USING THIS PRODUCT]
do not exceed recommended dosage
do not take for a long period of time
administer to children under the guidance and supervision of a guardian
avoid alcoholic drinks
do not drive a motor vehicle or operate machinery
barbiturates, tricyclic antidepressants, and alcohol may reduce the ability to metabolize large
quantities of acetaminophen, thereby increasing the plasma half-life of acetaminophen
myopathy may occur due to aldosteronism or hypokalemia when administered with drugs
containing potassium, licorice, glycyrrhizin acid or its salts, loop diuretics (furosemide,
ethacrynic acid) or thiazide diuretic (trichlormethiazide).

for oral administration